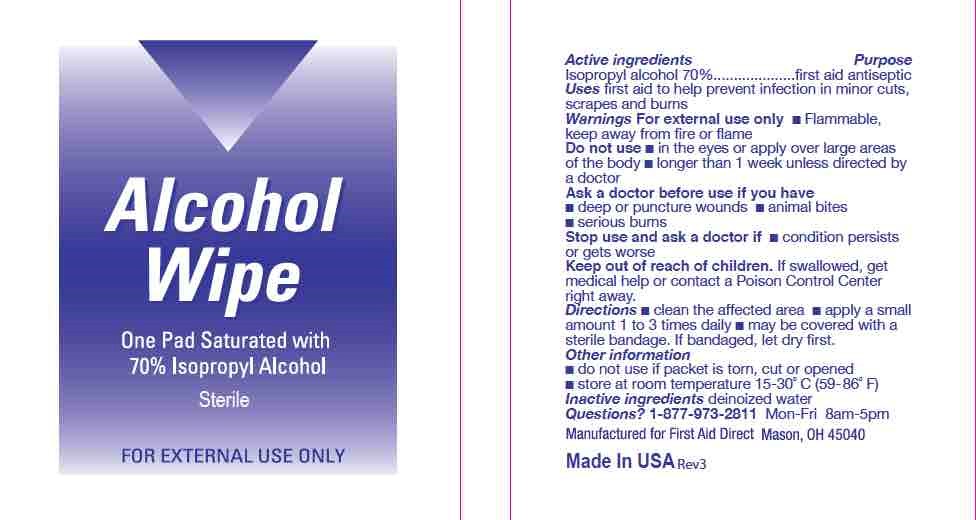 DRUG LABEL: Xpect Alcohol Wipes
NDC: 42961-019 | Form: SPONGE
Manufacturer: Cintas Corporation
Category: otc | Type: HUMAN OTC DRUG LABEL
Date: 20200910

ACTIVE INGREDIENTS: ISOPROPYL ALCOHOL .7 1/.7 mL
INACTIVE INGREDIENTS: WATER

Xpect Alcohol Wipes

Warnings

For External Use Only

Flammable, keep away from fire or flame

Do not use

- in eyes or apply over large areas of the body
- longer than 1 week unless directed by a doctor

Ask a doctor before use if you have

- deep or puncture wounds
- animal bites
- serious burns

Stop use and ask a doctor if

- condition persists or gets worse

Keep out of reach of children

- If swallowed, get medical help or contact a Poison Control Center right away

Directions

Clean the affected area
Apply a small amount 1 to 3 times daily
May be covered with a sterile bandage, if bandaged, let dry first

Uses

First aid to help prevent infection in minor cuts, scrapes, and burns

Other Information

Do not use if packet is torn, cut, or opened

Store at room temperature 15-30C (59-86F).

Questions?

1-877-973-2811 Monday-Friday 8:00am-5:00pm

Active Ingredients

Isopropyl alcohol 70%.....................first aid antiseptic

Uses

first aid to help prevent infection in minor cuts, scrapes, and burns.

KEEP OUT OF REACH OF CHILDREN

If swallowed get medical help or contact a poison control center right away.